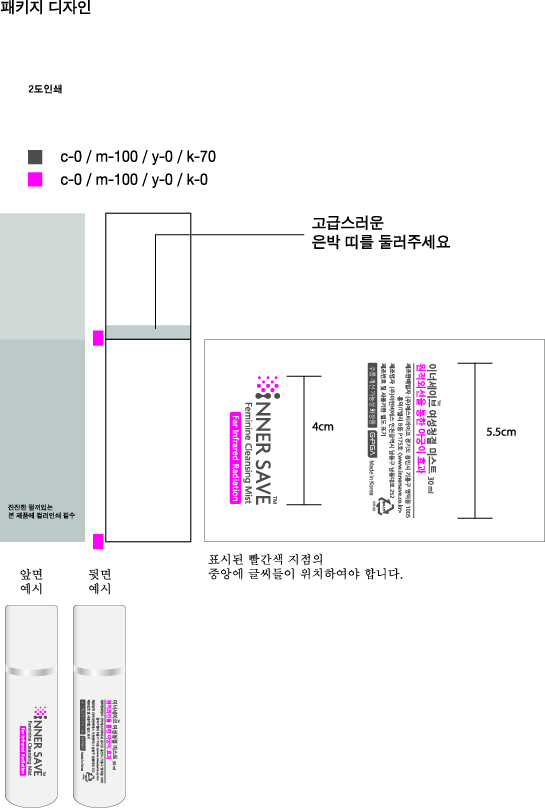 DRUG LABEL: INNER SAVE Feminine Cleansing Mist
NDC: 72068-0001 | Form: LIQUID
Manufacturer: ST Life Co.,Ltd.
Category: otc | Type: HUMAN OTC DRUG LABEL
Date: 20200103

ACTIVE INGREDIENTS: ADENOSINE 15 g/100 mL
INACTIVE INGREDIENTS: ALOE VERA LEAF; GLYCERIN

ACTIVE INGREDIENT

Adenosine

INACTIVE INGREDIENT

Cypress leaf extract, Mugwort extract, Aloe vera leaf water, Rosemary leaf extract, Butylene glycol, Glycerin, Sodium hyaluronate, Polyglutamic acid, Clofenine, Niacinamide, Anise extract, Grapefruit extract, Lotus extract, Paeoniasuffruticosa extract, Gold extract, Arginine, Dimethysulfone, Ethylhexyl glycerin, Lactic acid, Sorbitan herb extract, Citric acid, Ascorbic acid, Menthol

PURPOSE

Wrinkle repair

keep out or reach of the children

INDICATIONS AND USAGE

Take the proper amount of this product and apply to the skin.

[Warning]

Stop use and ask a doctor if you have irritations such as red spot, swallowing, and itching when using this product
Avoid using in the wounded area
Warning when storing

Keep out of reach of children
Avoid direct sunlight

In case of any abnormality in this product, you will get compensated according to the Fair Trade Commission Notice of Consumer Dispute Resolution Standards.

Customer Service Center +82-31-8065-4770 Serial Number and Expiration Date Written on the Bottle

DOSAGE AND ADMINISTRATION

for external use only